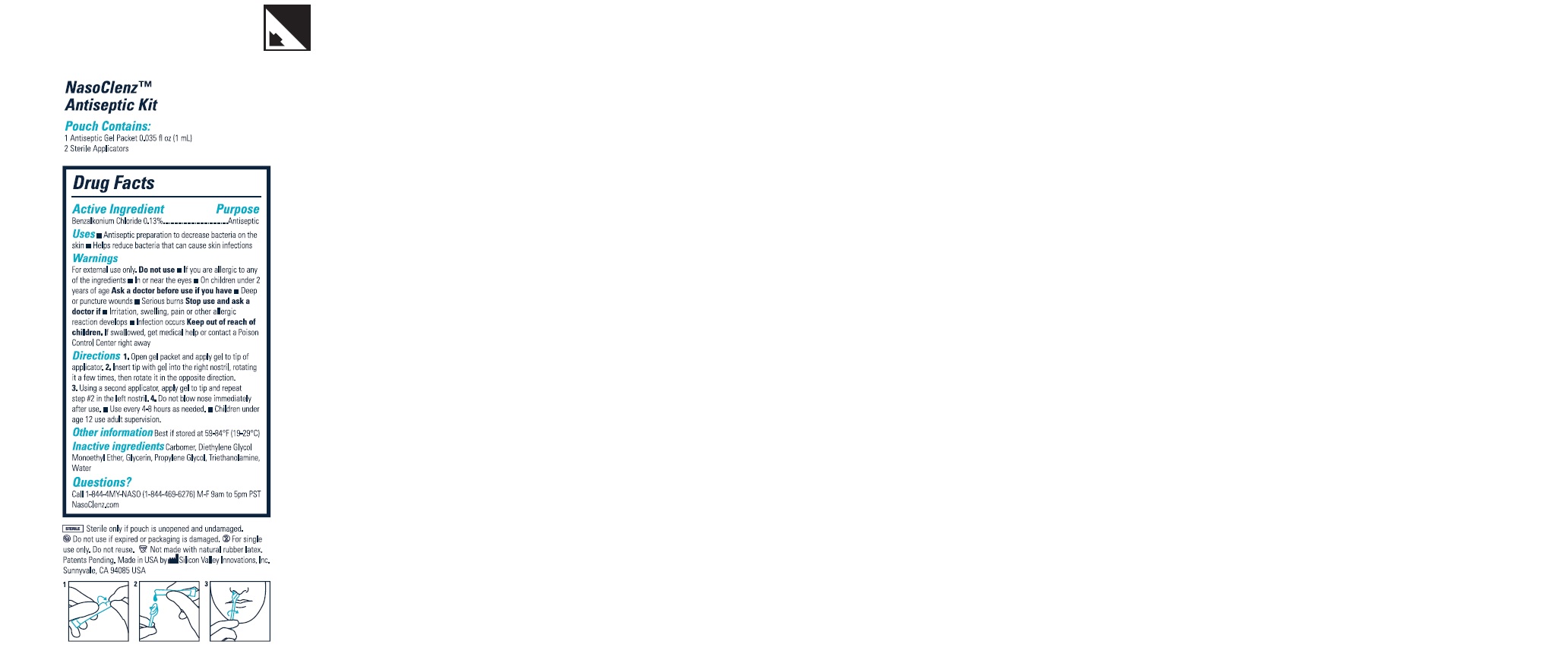 DRUG LABEL: Nasoclenz
NDC: 81900-013 | Form: GEL
Manufacturer: Silicon Valley Innovations, Inc.
Category: otc | Type: HUMAN OTC DRUG LABEL
Date: 20210707

ACTIVE INGREDIENTS: BENZALKONIUM CHLORIDE 1.19 mg/1 mL
INACTIVE INGREDIENTS: DIETHYLENE GLYCOL MONOETHYL ETHER 126 mg/1 mL; WATER 378 mg/1 mL; TROLAMINE 8.51 mg/1 mL; CARBOMER HOMOPOLYMER TYPE A (ALLYL PENTAERYTHRITOL CROSSLINKED) 5.67 mg/1 mL; PROPYLENE GLYCOL 63 mg/1 mL; GLYCERIN 677.19 mg/1 mL

Active Ingredient

Benzalkonium chloride (0.13%)

Uses

- Helps reduce bacteria that can cause skin infections

INDICATIONS AND USAGE

- Antiseptic preparation to decrease bacteria on skin

Warnings

For external use only.

Do Not Use

- If you are allegic to any of the ingredients
- In or near eyes
- On children under 2 years of age

Ask a doctor before use if you have

- Deep or puncture wounds
- Serious burns

Stop use and ask a doctor if

- Irritation, swelling, pain or other allergic reaction develops
- Infection occurs

Keep out of reach of children

If swallowed, get medical help or contact a Poison Control Center right away

Directions

1. Open gel packets and apply gel to tip of applicator
2. Insert tip with gel into the right nostril, rotating it a few times, then rotate it in the opposite direction.
3. Using a second applicator, apply gel to tip and repeat step #2 in the left nostril
4. Do not blow nose immediately after use.

DOSAGE AND ADMINISTRATION

- Use every 4-8 hours as needed
- Children under age 12 use adult supervision

Other information

Best if stored at 59-84F (19-29C)

Inactive Ingredients

Carbomer, Diethylene Glycol Monoethyl Ether, Glycerin, Propylene Glycol, Triethanolamine, Water

Questions?

Call 1-844-4MY-NASO (1-844-469-6276) M-F 9am to 5pm PST

Nasoclenz.com